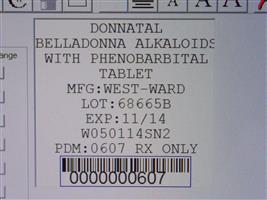 DRUG LABEL: Donnatal
NDC: 68151-0607 | Form: TABLET
Manufacturer: Carilion Materials Management
Category: prescription | Type: HUMAN PRESCRIPTION DRUG LABEL
Date: 20131203

ACTIVE INGREDIENTS: PHENOBARBITAL 16.2 mg/1 1; HYOSCYAMINE SULFATE 0.1037 mg/1 1; ATROPINE SULFATE 0.0194 mg/1 1; SCOPOLAMINE HYDROBROMIDE 0.0065 mg/1 1
INACTIVE INGREDIENTS: ANHYDROUS LACTOSE; CALCIUM STEARATE; SILICON DIOXIDE; STARCH, CORN; CELLULOSE, MICROCRYSTALLINE

Donnatal Tablets

Description

Each Donnatal® Tablet contains:

Phenobarbital, USP....................................... 16.2 mg

Hyoscyamine Sulfate, USP...................... 0.1037 mg

Atropine Sulfate, USP ...............................0.0194 mg

Scopolamine Hydrobromide, USP ...........0.0065 mg

INACTIVE INGREDIENTS: Anhydrous Lactose, Calcium Stearate, Colloidal

Silicon Dioxide, Corn Starch, and Microcrystalline Cellulose.

INACTIVE INGREDIENTS

Anhydrous Lactose, Calcium Stearate, Colloidal Silicon Dioxide, Corn Starch, and Microcrystalline Cellulose

CLINICAL PHARMACOLOGY

This drug combination provides natural belladonna alkaloids in a specific, fixed ratio combined with phenobarbital to

provide peripheral anticholinergic/antispasmodic action and mild sedation.

INDICATIONS AND USAGE

Based on a review of this drug by the National Academy of Sciences-National Research Council and/or other

information, FDA has classified the following indications as “possibly” effective:

For use as adjunctive therapy in the treatment of irritable bowel syndrome (irritable colon, spastic colon, mucous colitis)

and acute enterocolitis.

May also be useful as adjunctive therapy in the treatment of duodenal ulcer. IT HAS NOT BEEN SHOWN

CONCLUSIVELY WHETHER ANTICHOLINERGIC/ANTISPASMODIC DRUGS AID IN THE HEALING OF A

DUODENAL ULCER, DECREASE THE RATE OF RECURRENCES OR PREVENT COMPLICATIONS.

CONTRAINDICATIONS

Glaucoma, obstructive uropathy (for example, bladder neck obstruction due to prostatic hypertrophy); obstructive

disease of the gastrointestinal tract (as in achalasia, pyloroduodenal stenosis, etc.); paralytic ileus, intestinal atony of

the elderly or debilitated patient; unstable cardiovascular status in acute hemorrhage; severe ulcerative colitis

especially if complicated by toxic mega-colon; myasthenia gravis; hiatal hernia associated with reflux esophagitis.

Donnatal® is contraindicated in patients with known hypersensitivity to any of the ingredients. Phenobarbital is

contraindicated in acute intermittent porphyria and in those patients in whom phenobarbital produces restlessness

and/or excitement.

WARNINGS

In the presence of a high environmental temperature, heat prostration can occur with belladonna alkaloids (fever and

heatstroke due to decreased sweating).

Diarrhea may be an early symptom of incomplete intestinal obstruction, especially in patients with ileostomy or

colostomy. In this instance, treatment with this drug would be inappropriate and possibly harmful.

Donnatal® may produce drowsiness or blurred vision. The patient should be warned, should these occur, not to

engage in activities requiring mental alertness, such as operating a motor vehicle or other machinery, and not to

perform hazardous work.

Phenobarbital may decrease the effect of anticoagulants, and necessitate larger doses of the anticoagulant for optimal

effect. When the phenobarbital is discontinued, the dose of the anticoagulant may have to be decreased.

Phenobarbital may be habit forming and should not be administered to individuals known to be addiction prone or to

those with a history of physical and/or psychological dependence upon drugs.

Since barbiturates are metabolized in the liver, they should be used with caution and initial doses should be small in

patients with hepatic dysfunction.

PRECAUTIONS

Use with caution in patients with: autonomic neuropathy, hepatic or renal disease, hyperthyroidism, coronary heart

disease, congestive heart failure, cardiac arrhythmias, tachycardia, and hypertension.

Belladonna alkaloids may produce a delay in gastric emptying (antral stasis) which would complicate the management

of gastric ulcer.

Do not rely on the use of the drug in the presence of complication of biliary tract disease.

Theoretically, with overdosage, a curare-like action may occur.

CARCINOGENESIS, MUTAGENESIS, IMPAIRMENT OF FERTILITY

Long-term studies in animals have not been performed to evaluate carcinogenic potential.

PREGNANCY

PREGNANCY CATEGORY C

Animal reproduction studies have not been conducted with Donnatal®. It is not known whether Donnatal® can cause

fetal harm when administered to a pregnant woman or can affect reproduction capacity. Donnatal® should be given to

a pregnant woman only if clearly needed.

NURSING MOTHERS

It is not known whether this drug is excreted in human milk. Because many drugs are excreted in human milk, caution

should be exercised when Donnatal® is administered to a nursing woman.

ADVERSE REACTIONS

Adverse reactions may include xerostomia; urinary hesitancy and retention; blurred vision; tachycardia; palpitation;

mydriasis; cycloplegia; increased ocular tension; loss of taste sense; headache; nervousness; drowsiness; weakness;

dizziness; insomnia; nausea; vomiting; impotence; suppression of lactation; constipation; bloated feeling;

musculoskeletal pain; severe allergic reaction or drug idiosyncrasies, including anaphylaxis, urticaria and other dermal

manifestations; and decreased sweating. Acquired hypersensitivity to barbituates consists chiefly in allergic reactions

that occur especially in persons who tend to have asthma, urticaria, angiodema and similar conditions. Hypersensitivity

reactions in this category include localized swelling, particularly of the eyelids, cheeks, or lips, and erythematous

dermatitis. Rarely, exfoliative dermatitis (e.g. Stevens-Johnson syndrome and toxic epidermal necrolysis) may be

caused by phenobarbital and can prove fatal. The skin eruption may be associated with fever, delirium, and marked

degenerative changes in the liver and other parenchymatous organs. In a few cases, megaloblastic anemia has been

associated with the chronic use of phenobarbital. Elderly patients may react with symptoms of excitement, agitation,

drowsiness, and other untoward manifestations to even small doses of the drug. Phenobarbital may produce

excitement in some patients, rather than a sedative effect. In patients habituated to barbiturates, abrupt withdrawal

may produce delirium or convulsions.

DOSAGE AND ADMINISTRATION

The dosage of Donnatal® should be adjusted to the needs of the dividual patient to assure symptomatic control with a

minimum of adverse effects.

Donnatal® Tablets. Adults: One or two Donnatal® tablets three or four times a day according to condition and severity

of symptoms.

OVERDOSAGE

The signs and symptoms of overdose are headache, nausea, vomiting, blurred vision, dilated pupils, hot and dry skin,

dizziness, dryness of the mouth, difficulty in swallowing, and CNS stimulation. Treatment should consist of gastric

lavage, emetics, and activated charcoal. If indicated, parenteral cholinergic agents such as physostigmine or

bethanechol chloride, should be used.

How Supplied

NDC:68151-0607-1 in a PACKAGE of 1 TABLETS